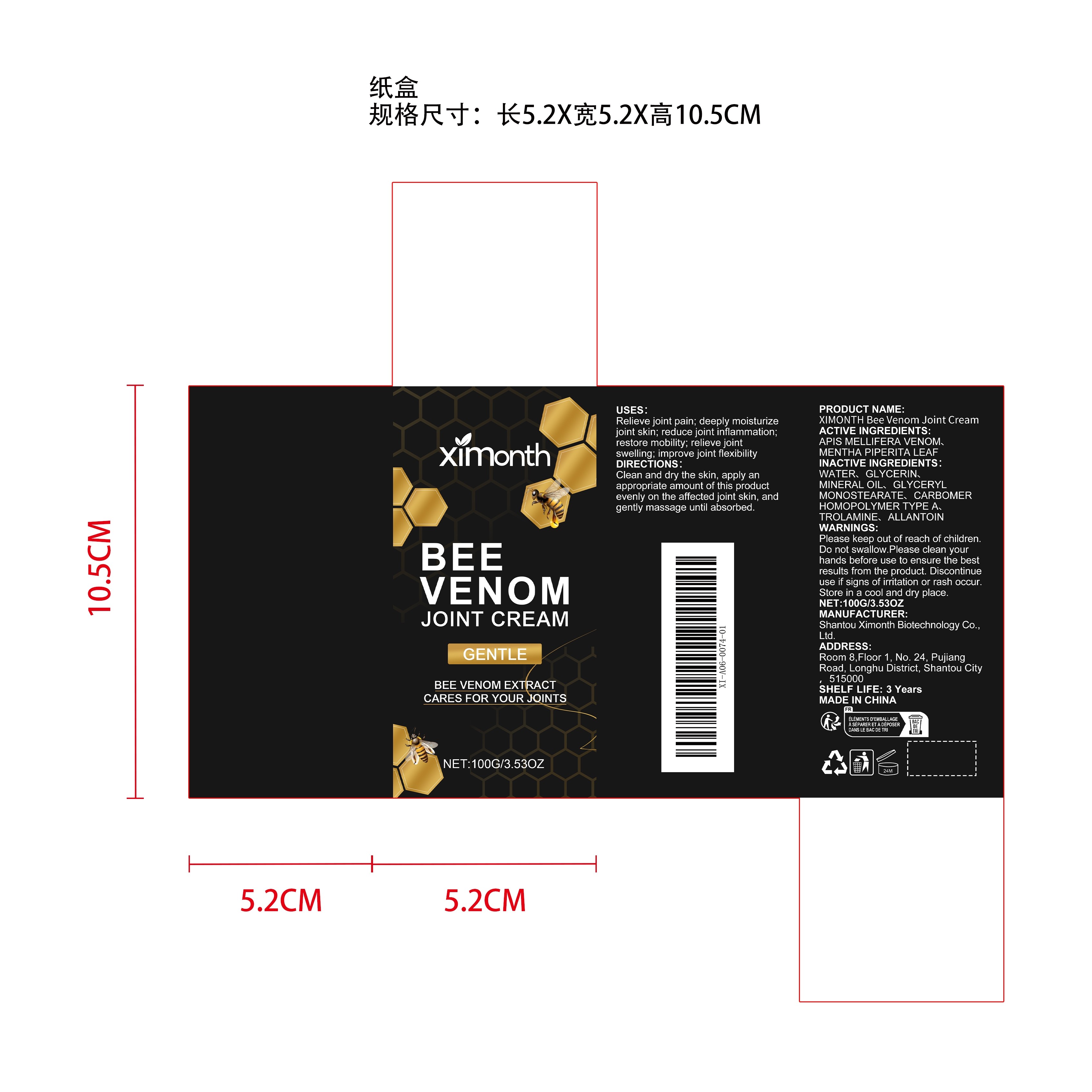 DRUG LABEL: XIMONTH Bee Venom Joint Cream
NDC: 84989-005 | Form: CREAM
Manufacturer: Shantou Ximonth Biotechnology Co., Ltd.
Category: otc | Type: HUMAN OTC DRUG LABEL
Date: 20251126

ACTIVE INGREDIENTS: APIS MELLIFERA VENOM 0.02 mg/100 mg; MENTHA PIPERITA LEAF 0.02 mg/100 mg
INACTIVE INGREDIENTS: GLYCERIN 8 mg/100 mg; MINERAL OIL 5 mg/100 mg; GLYCERYL MONOSTEARATE 2 mg/100 mg; TROLAMINE 0.2 mg/100 mg; ALLANTOIN 0.02 mg/100 mg; WATER 84.54 mg/100 mg; CARBOMER HOMOPOLYMER TYPE A 0.2 mg/100 mg

ACTIVE INGREDIENT

APIS MELLIFERA VENOM、MENTHA PIPERITA LEAF

PURPOSE

1. Deeply moisturizes and keeps skin soft for a long time.

2. Soothes skin and relieves dryness and discomfort.

3. Gentle formula, suitable for daily use.

4. Quickly absorbed, light and non-greasy.

WHEN USING

Clean and dry the skin, apply an appropriate amount of this product evenly on the affected joint skin, and gently massage until absorbed.

STOP USE

Discontinue use if signs of irritation or rash occur.

DO NOT USE

Discontinue use if signs of irritation or rash occur.

KEEP OUT OF REACH OF CHILDREN

Please keep out of reach of children. Do not swallow.

WARNINGS

Please keep out of reach of children. Do not swallow.Please clean your hands before use to ensure the best results from the product. Discontinue use if signs of irritation or rash occur. Store in a cool and dry place.

STORAGE AND HANDLING

Store in a cool and dry place.

INACTIVE INGREDIENT

WATER、GLYCERIN、MINERAL OIL、GLYCERYL MONOSTEARATE、CARBOMER HOMOPOLYMER TYPE A、TROLAMINE、ALLANTOIN